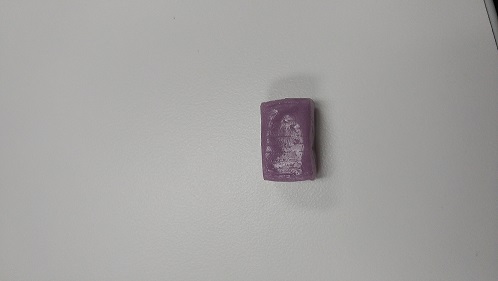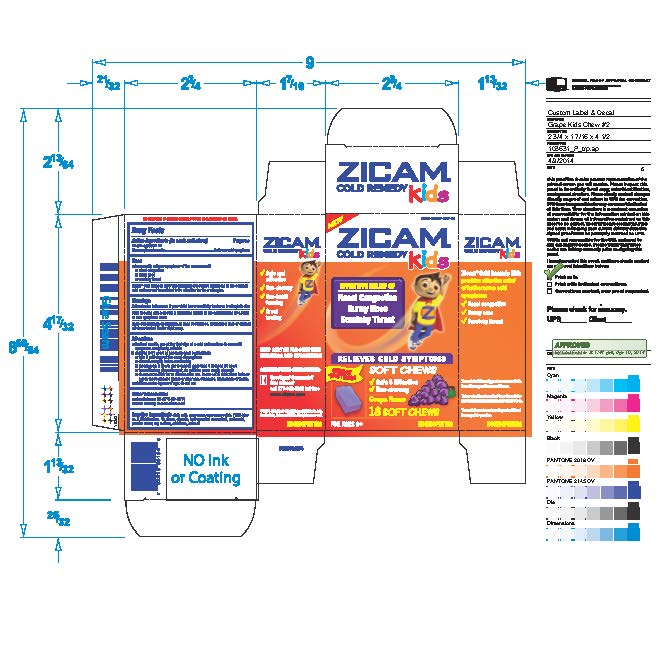 DRUG LABEL: Zicam Kids Cold Relief Remedy
NDC: 52642-231 | Form: TABLET, CHEWABLE
Manufacturer: BestCo Inc.
Category: homeopathic | Type: HUMAN OTC DRUG LABEL
Date: 20160224

ACTIVE INGREDIENTS: ZINC ACETATE 3.54 mg/1 1; ZINC GLUCONATE 4.5 mg/1 1
INACTIVE INGREDIENTS: SUCROSE

Zincum aceticum 2X
Zincum gluconicum 2X

Active ingredients (in each soft chew)

Zincum aceticum 2X

Zincum gluconicum 2X

Purpose

Relieves cold symptoms

Uses

- temporarily relieves symptoms of the common cold
- nasal congestion
- runny nose
- scratchy throat

WARNINGS

Zicam Cold Remedy Relief KIDS was formulated to relieve symptoms of the common cold and was not formulated to be effective for flu or allergies.

Ask a doctor before use if your child has a sensitivity to zinc or is allergic to zinc.

Stop use and ask a doctor if symptoms persist or are accompanied by a fever or new symptoms occur

Keep out of reach of children.

OVERDOSAGE

In case of overdose, get medical help or contact a Poison Control Center right away.

Directions

- for best results, use at the first sign of a cold and continue to use until symptoms completely subside
- children 6-11 years of age (with adult supervision)
- take 1 soft chew at the onset of symptoms
- chew thoroughly before swallowing
- repeat every 3 hours; not to exceed more than 4 doses in 24 hours
- to avoid minor stomach upset, do not take on an empty stomach
- do not eat or drink for 15 minutes after use. Do not eat or drink citrus fruits or juices for 30 minutes before or after use. Otherwise, drink plenty of fluids.
- children under 6 years of age; do not use.

Other information

- store between 15-29C (59-84F)
- avoid freezing and excessive heat

Inactive ingredients

citric acid, corn syrup, corn syrup solids, FD&C blue no. 1, FD&C red no. 40, flavor, glycerin, hydrogenated coconut oil, malic acid, purified water, soy lecithin, sucralose, sucrose